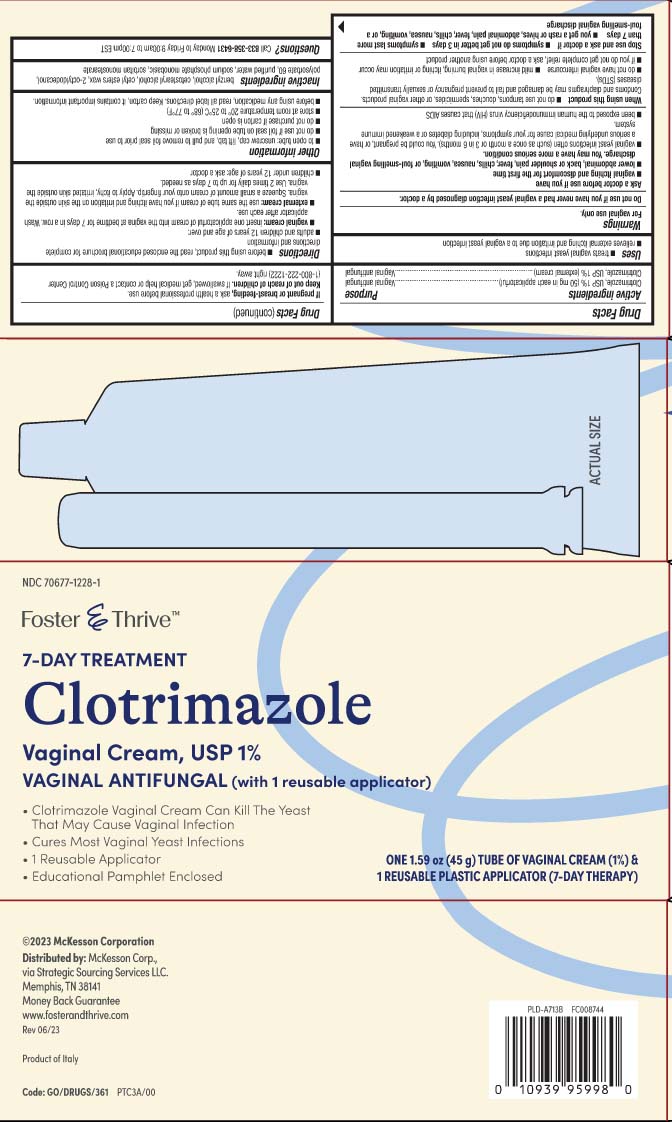 DRUG LABEL: Clotrimazole
NDC: 70677-1228 | Form: CREAM
Manufacturer: Strategic Sourcing Services LLC
Category: otc | Type: HUMAN OTC DRUG LABEL
Date: 20260127

ACTIVE INGREDIENTS: CLOTRIMAZOLE 10 mg/1 g
INACTIVE INGREDIENTS: BENZYL ALCOHOL; CETOSTEARYL ALCOHOL; CETYL ESTERS WAX; OCTYLDODECANOL; POLYSORBATE 60; WATER; SODIUM PHOSPHATE, MONOBASIC, MONOHYDRATE; SORBITAN MONOSTEARATE

Clotrimazole Vaginal Cream, USP

Active ingredient

Clotrimazole, USP 1% (50 mg in each applicatorful)

Clotrimazole, USP 1% (external cream)

Purpose

Vaginal antifungal

Vaginal antifungal

Uses

- treats vaginal yeast infections
- relieves external itching and irritation due to a vaginal yeast infection

Warnings

For external use only.

Do not use

if you have never had a vaginal yeast infection diagnosed by a doctor.

Ask a doctor before use if you have

- vaginal itching and discomfort for the first time
- lower abdominal, back or shoulder pain, fever, chills nausea, vomiting, or foul-smelling vaginal discharge. You may have a more serious condition.
- vaginal yeast infections often (such as once a month or 3 in 6 months). You could be pregnant, or have a serious underlying medical cause for your symptoms, including diabetes or a weakened immune system.
- been exposed to the human immunodeficiency virus (HIV) that causes AIDS

When using this product,

- do not use tampons, douches, spermicides, or other vaginal products. Condoms and diaphragms may be damaged and fail to prevent pregnancy or sexually transmitted diseases (STDs).
- do not have vaginal intercourse
- mild increase in vaginal burning, itching or irritation may occur
- if you do not get complete relief, ask a doctor before using another product

Stop use and ask a doctor if

- symptoms do not get better in 3 days
- symptoms last more than 7 days
- you get a rash or hives, abdominal pain, fever, chills, nausea, vomiting, or a foul-smelling vaginal dischage

If pregnant or breast-feeding,

ask a health professional before use.

Keep out of reach of children.

If swallowed, get medical help or contact a Poison Control Center (1-800-222-1222) right away.

Directions

- before using this product, read the enclosed educational brochure for complete directions and information
- adults and children 1 years of age and over:
  - vaginal cream: insert one applicatorful of cream into the vagina at bedtime for 7 days in a row. Wash applicator after each use.
  - external cream: use the same tube of cream if you have itching and irritation on the skin outside the vagina. Squeeze a small amount of cream onto your fingertip. Apply to itchy, irritated skin outside the vagina. Use 2 times daily for up to 7 days as needed.
- children under 12 years of age: ask a doctor

Other information

- to open tube: unscrew cap, lift tab, and pull to remove foil seal prior to use
- do not use if foil seal on tube opening is broken or missing
- do not purchase if carton is open
- store at room temperature 20º to 25ºC (68º to 77ºF)
- before using any medication, read all label directions. Keep carton, it contain important information.

Inactive ingredients

benzyl alcohol, cetostearyl alcohol, cetyl esters wax, 2-octyldodecanol, polysorbate 60, purified water, sodium phosphate monobasic, sorbitan monostearate

Questions or comments?

Call 1-833-358-6431 Monday to Friday 9:00am to 7:00pm EST

Principal display panel

7-DAY TREATMENT

Clotrimazole

Vaginal Cream, USP 1%

VAGINAL ANTIFUNGAL (with 1 reusable applicator)

- Clotrimazole Vaginal Cream Can Kill The Yeast That May Cause Vaginal Infection
- Cures Most Vaginal Yeast Infections
- 1 Reusable Applicator
- Educational Pamphlet Enclosed

Distributed by: McKesson Corp.,

via Strategic Sourcing Services LLC.

Memphis, TN 38141

Package label

FOSTER & THRIVE Vaginal Cream